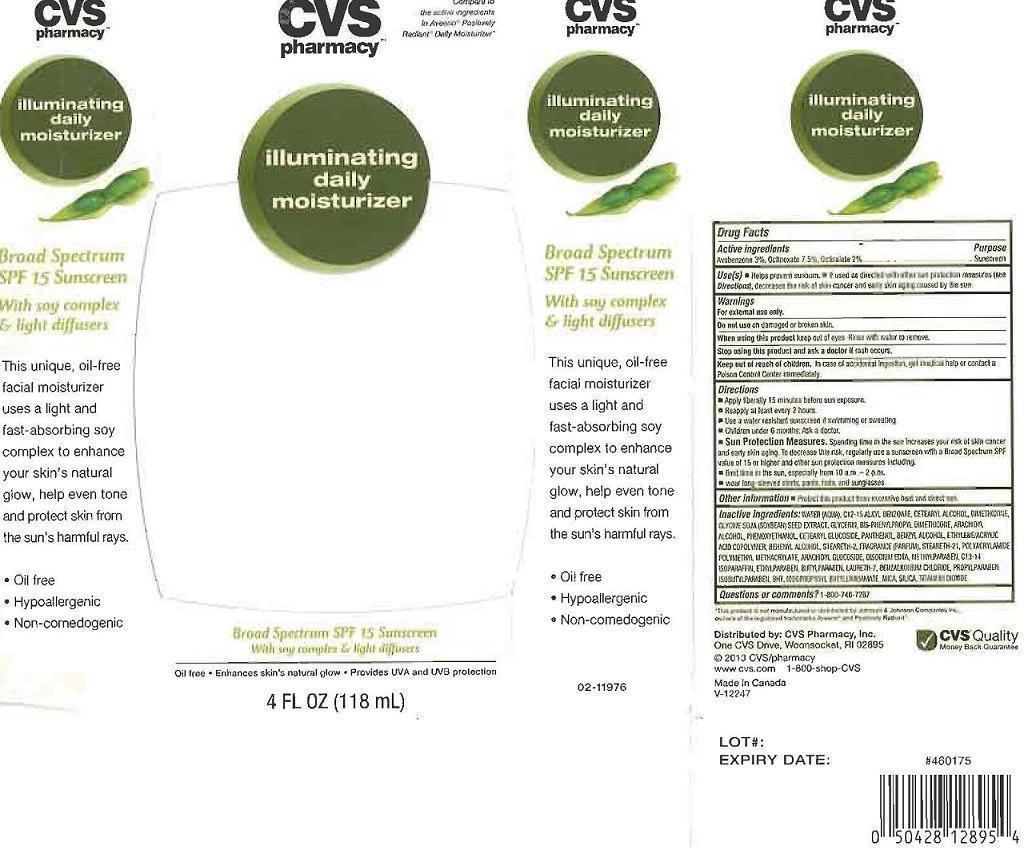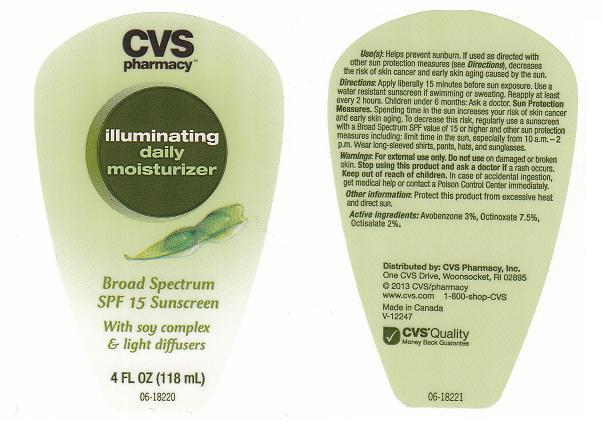 DRUG LABEL: CVS PHARMACY
NDC: 59779-602 | Form: LOTION
Manufacturer: CVS PHARMACY
Category: otc | Type: HUMAN OTC DRUG LABEL
Date: 20130614

ACTIVE INGREDIENTS: AVOBENZONE 30 mg/1 mL; OCTINOXATE 75 mg/1 mL; OCTISALATE 20 mg/1 mL
INACTIVE INGREDIENTS: WATER; C12-15 ALKYL BENZOATE; CETOSTEARYL ALCOHOL; DIMETHICONE; SOYBEAN; GLYCERIN; DIMETHICONE PEG-15 ACETATE; ARACHIDYL ALCOHOL; PHENOXYETHANOL; CETEARYL GLUCOSIDE; PANTHENOL; BENZYL ALCOHOL; TRIMETHYLOLPROPANE TRIACRYLATE; DOCOSANOL; STEARETH-2; STEARETH-21; POLYACRYLAMIDE (10000 MW); METHYL METHACRYLATE; ARACHIDYL GLUCOSIDE; EDETATE DISODIUM; METHYLPARABEN; C13-14 ISOPARAFFIN; ETHYLPARABEN; BUTYLPARABEN; LAURETH-7; BENZALKONIUM CHLORIDE; PROPYLPARABEN; ISOBUTYLPARABEN; BUTYLATED HYDROXYTOLUENE; IODOPROPYNYL BUTYLCARBAMATE; MICA; SILICON DIOXIDE; TITANIUM DIOXIDE

DRUG FACTS

ACTIVE INGREDIENTS

AVOBENZONE 3%, OCTINOXATE 7.5%, OCTISALATE 2%

PURPOSE

SUNSCREEN

USE(S)

HELPS PREVENT SUNBURN. IF USED AS DIRECTED WITH OTHER SUN PROTECTION MEASURES (SEE DIRECTIONS), DECREASES THE RISK OF SKIN CANCER AND EARLY SKIN AGING CAUSED BY THE SUN.

WARNINGS

FOR EXTERNAL USE ONLY.

DO NOT USE

ON DAMAGED OR BROKEN SKIN.

WHEN USING THIS PRODUCT

KEEP OUT OF EYES. RINSE WITH WATER TO REMOVE.

STOP USING THIS PRODUCT AND ASK A DOCTOR IF

RASH OCCURS.

KEEP OUT OF REACH OF CHILDREN

IN CASE OF ACCIDENTAL INGESTION, GET MEDICAL HELP OR CONTACT A POISON CONTROL CENTER IMMEDIATELY.

DIRECTIONS

APPLY LIBERALLY 15 MINUTES BEFORE SUN EXPOSURE. REAPPLY AT LEAST EVERY 2 HOURS. USE A WATER RESISTANT SUNSCREEN IF SWIMMING OR SWEATING. CHILDREN UNDER 6 MONTHS: ASK A DOCTOR.

SUN PROTECTION MEASURES

SPENDING TIME IN THE SUN INCREASES YOUR RISK OF SKIN CANACER AND EARLY SKIN AGING. TO DECREASE THIS RISK, REGULARLY USE A SUNSCREEN WITH A BROAD SPECTRUM SPF VALUE OF 15 OR HIGHER AND OTHER SUN PROTECTION MEASURES INCLUDING: LIMIT TIME IN THE SUN, ESPECIALLY FROM 10 A.M. - 2 P.M. WEAR LONG-SLEEVED SHIRTS, PANTS, HATS, AND SUNGLASSES.

OTHER INFORMATION

PROTECT THIS PRODUCT FROM EXCESSIVE HEAT AND DIRECT SUN.

INACTIVE INGREDIENTS:

WATER (AQUA), C12-15 ALKYL BENZOATE, CETEARYL ALCOHOL, DIMETHICONE, GLYCINE SOJA (SOYBEAN) SEED EXTRACT, GLYCERIN, BIS-PHENYLPROPYL DIMETHICONE, ARACHIDYL ALCOHOL, PHENOXYETHANOL, CETEARYL GLUCOSIDE, PANTHENOL, BENZYL ALCOHOL, ETHYLENE/ACRYLIC ACID COPOLYMER, BEHENYL ALCOHOL, STEARETH-2, FRAGRANCE (PARFUM), STEARETH-21, POLYACRYLAMIDE, POLYMETHYL METHACRYLATE, ARACHIDYL GLUCOSIDE, DISODIUM EDTA, METHYLPARABEN, C13-14 ISOPARAFFIN, ETHYLPARABEN, BUTYLPARABEN, LAURETH-7, BENZALKONIUM CHLORIDE, PROPYLPARABEN, ISOBUTYLPARABEN, BHT, IODOPROPYNYL BUTYLCARBAMATE, MICA, SILICA, TITANIUM DIOXIDE.

QUESTIONS OR COMMENTS?

1-800-746-7287